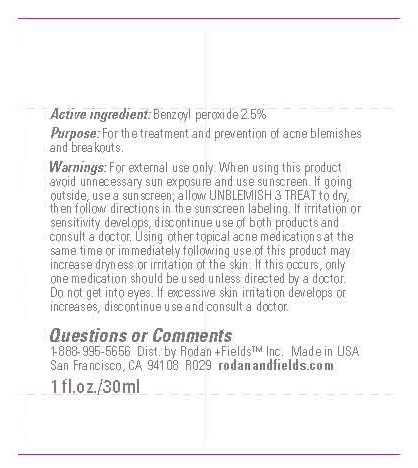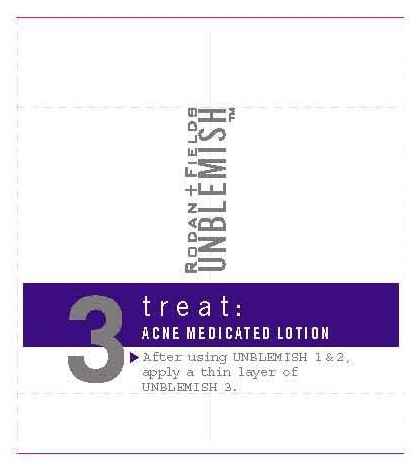 DRUG LABEL: Rodan and Fields
NDC: 56152-0010 | Form: CREAM
Manufacturer: Cosmetic Enterprises
Category: otc | Type: HUMAN OTC DRUG LABEL
Date: 20100723

ACTIVE INGREDIENTS: BENZOYL PEROXIDE 2.5 mL/100 mL

Unblemish - Acne Medicated Lotion

Active Ingredients

Benzoyl Peroxide 2.5%

WARNINGS

Warnings: For external use only. When using this product avoid unnecessary sun exposure and use sunscreen. If going outside, use a sunscreen; allow UNBLEMISH 4 TREAT to dry, then follow directions in the sunscreen labeling. If irritation or sensitivity develops, discontinue use of both products and consult a doctor. Using other topical acne medications at the same time or immediately following use of this product may increase dryness or irritation of the skin. If this occurs, only one medication should be used unless directed by a doctor. Do not get into eyes. If excessive skin irritation develops or increase, discontinue use and consult a doctor.

INDICATIONS AND USAGE

Purpose: For the treatment and prevention of acne blemishes and breakouts.

Questions or Comments

1-888-995-5656

PACKAGE LABEL

Unblemish- Acne Medicated Lotion

1 fl. oz./6 mL